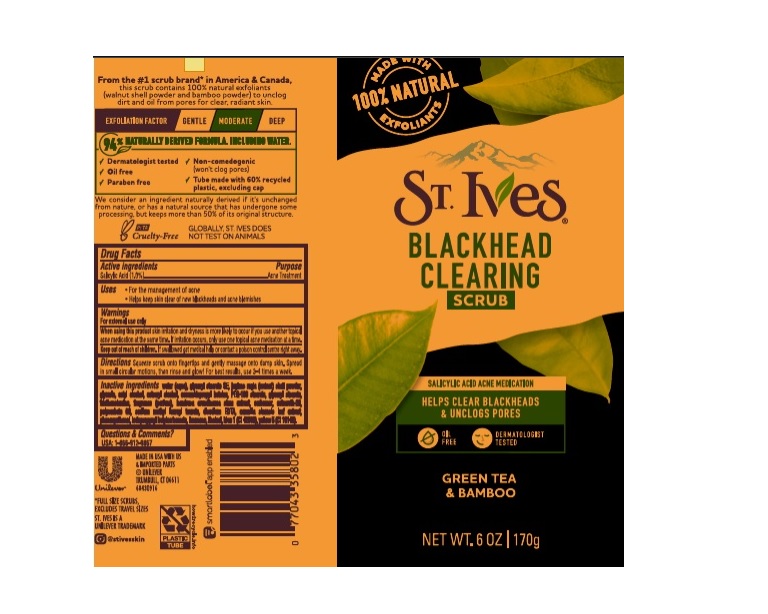 DRUG LABEL: St. Ives
NDC: 64942-1860 | Form: EMULSION
Manufacturer: CONOPCO Inc. d/b/a Unilever
Category: otc | Type: HUMAN OTC DRUG LABEL
Date: 20241025

ACTIVE INGREDIENTS: SALICYLIC ACID 0.01 g/1 g
INACTIVE INGREDIENTS: WATER; JUGLANS REGIA SHELL; GLYCERIN; SODIUM LAUROYL METHYL TAURATE; GREEN TEA LEAF; COCAMIDOPROPYL BETAINE; CETOSTEARYL ALCOHOL; TROLAMINE; CETYL ALCOHOL; PEG-100 STEARATE; BAMBUSA BAMBOS STEM; FD&C BLUE NO. 1; POLYOXYL 20 CETOSTEARYL ETHER; POLYSORBATE 60; FD&C YELLOW NO. 5; EDETATE DISODIUM ANHYDROUS; GLYCERYL MONOSTEARATE; IODOPROPYNYL BUTYLCARBAMATE; GLYCERYL STEARATE SE; PHENOXYETHANOL; CARBOMER HOMOPOLYMER, UNSPECIFIED TYPE; LINALOOL, (+/-)-; LIMONENE, (+)-

St. Ives Green Tea & Bamboo Blackhead Cleansing Scrub

ST. IVES GREEN TEA & BAMBOO BLACKHEAD CLEANSING SCRUB - (salicylic acid) emulsion

St. Ives Green Tea & Bamboo Blackhead Cleansing Scrub

Active ingredient

Salicylic Acid (1%)

Purpose

Acne Treatment

Uses

For the mangement of acne
Helps keep skin clear of new blackheads and acne blemishes

Warnings

For external use only
When using this product skin irritation and dryness is more likely to occur if you use another topical acne medication at the same time. If irritation occues, only use one topical acne medication at a time.
When using this product keep out of eyes. Rinse with water to remove

Keep out of reach of children
If swallowed, get medical help or contact a Poison Control Center right away.

Directions

Squeeze scrub onto fingertips and gently massage onto damp skin. Spread in small circular motions, then rinse and glow! For best results, use 3-4 times a week

Inactive ingredients

Water (Aqua), Glyceryl Stearate SE, Juglans Regia (Walnut) Shell Powder, Glycerin, Cetyl Alcohol, Cetearyl Alcohol, Cocamidopropyl Betaine, PEG-100 Stearate, Glyceryl Stearate, Triethanolamine, Fragrance (Parfum), Bambusa Arundinacea Stem Extract, Carbomer, Ceteareth-20, Polysorbate 60, Sodium Methyl Lauroyl Taurate, Disodium EDTA, Camellia Sinensis Leaf Extract, Phenoxyethanol, Iodopropynyl Butylcarbamate, Limonene, Linalool, Blue 1 (CI 42090), Yellow 5 (CI 19140).

Questions or comments?

USA: 1-800-912-9867